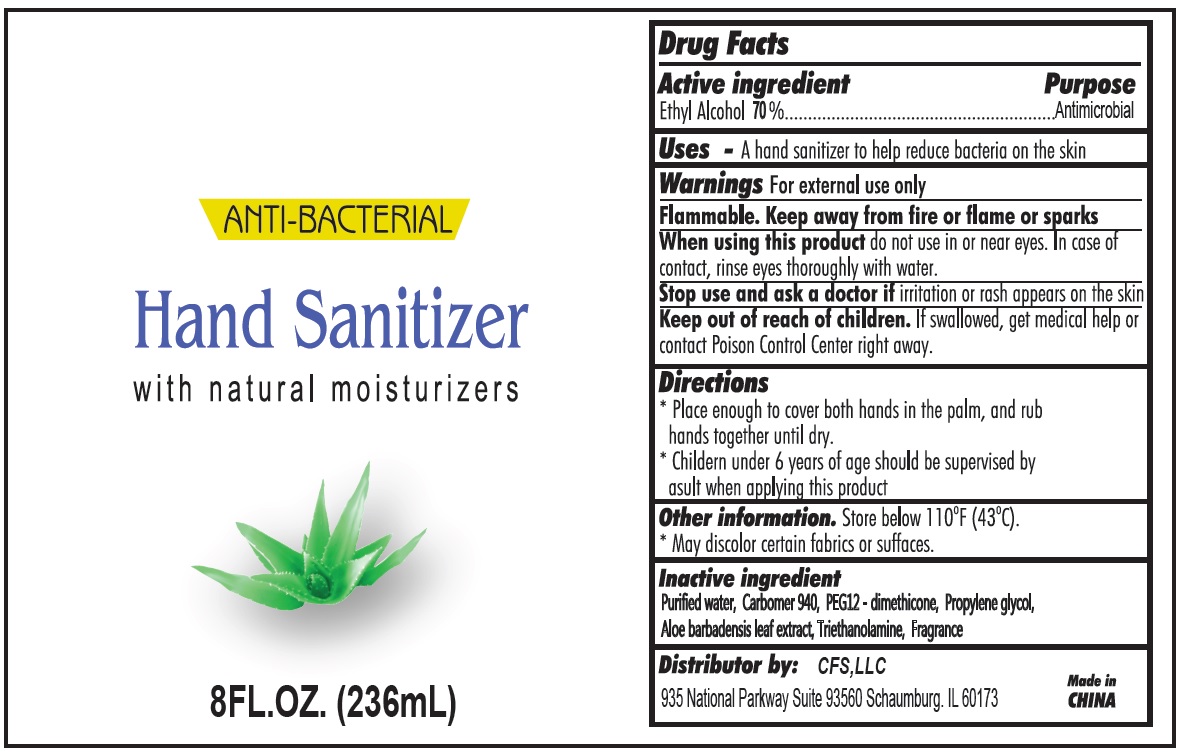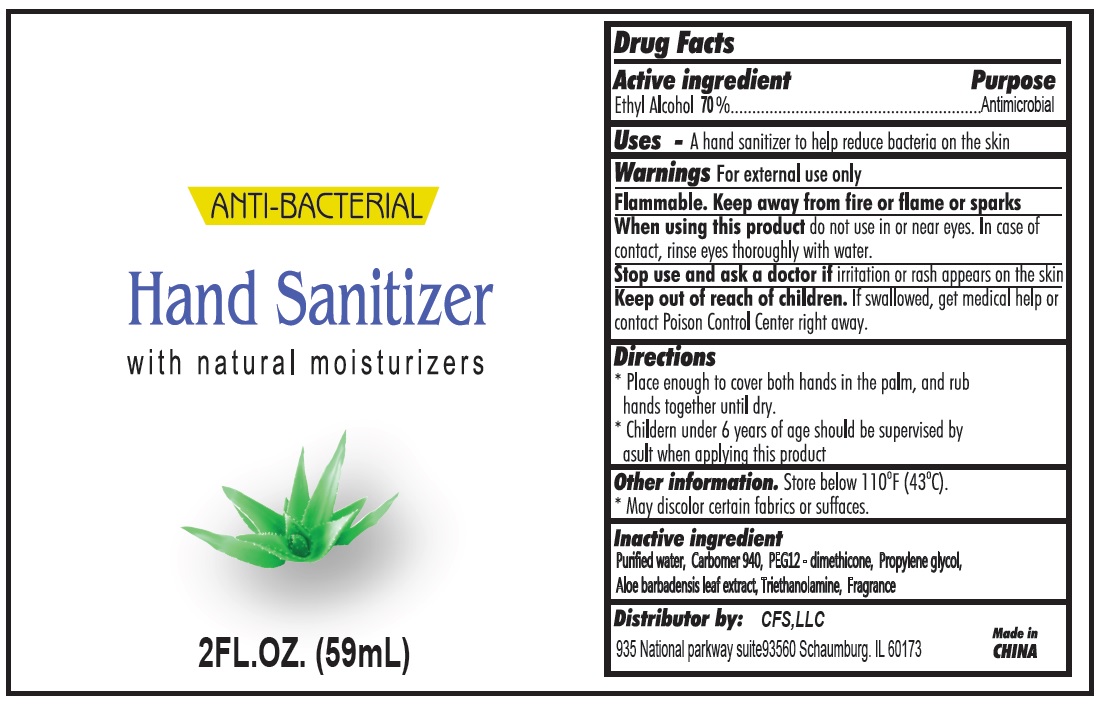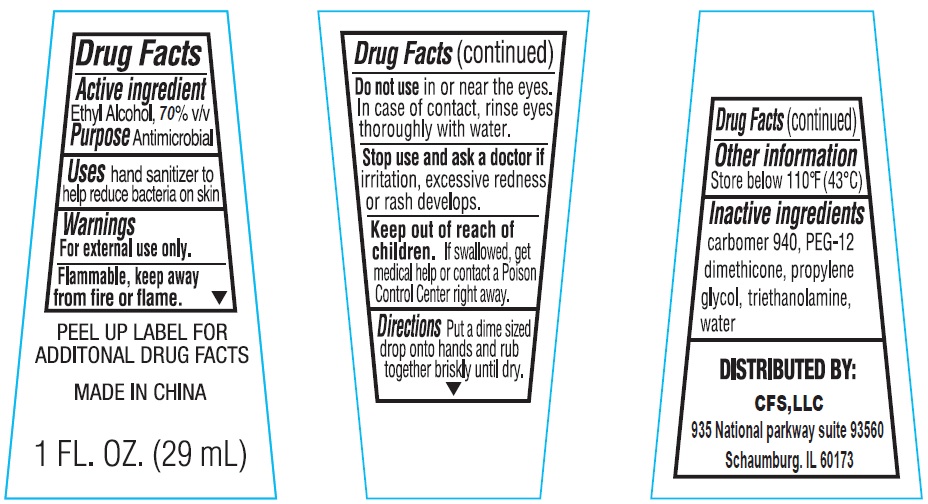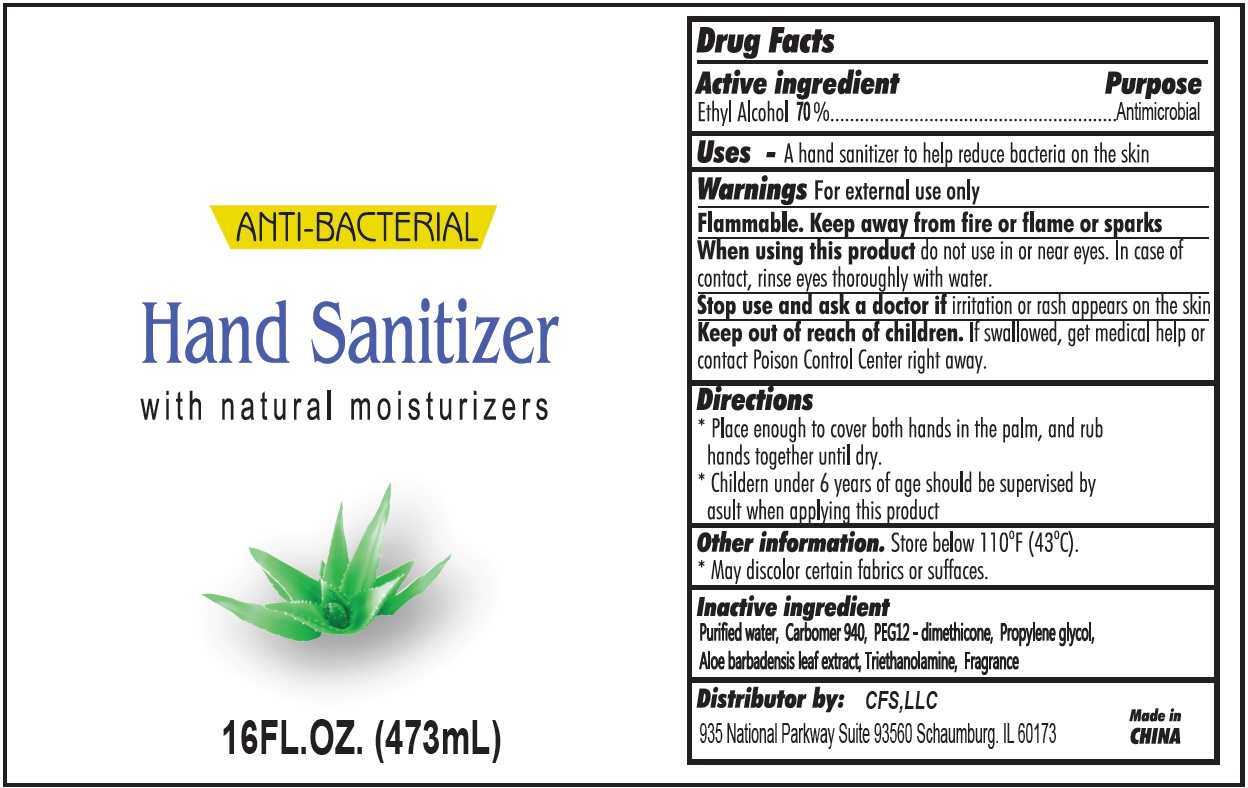 DRUG LABEL: Hand Sanitizer
NDC: 74649-000 | Form: GEL
Manufacturer: Yiwu Pharmacy Ecomm Business Enterprise Ltd
Category: otc | Type: HUMAN OTC DRUG LABEL
Date: 20200422

ACTIVE INGREDIENTS: ALCOHOL 0.7 mL/1 mL
INACTIVE INGREDIENTS: WATER; CARBOMER 940; PEG-12 DIMETHICONE (300 CST); PROPYLENE GLYCOL; ALOE VERA LEAF; TROLAMINE

Hand Sanitizer

Active ingredient

Ethyl Alcohol 70%

Purpose

Antimicrobial

Uses:

- A hand sanitizer to help reduce bacteria on the skin

Warnings:

For External Use Only.

Flammable. Keep away from fire or flame or sparks

When using this product

do not use in or near eyes. In case of contact, rinse eyes thoroughly with water.

Stop use and ask a doctor if

irritation or rash appears on the skin

Keep out of reach of children.

If swallowed, get immediate help or contact a Poison Control Center right away.

Directions:

- Place enough to cover both hands in the palm, and rub hands together until dry.
- Children under 6 years of age should be supervised by adult when applying this product.

Other information.

- Store below 110oF (43oC)
- May discolor certain fabrics or surfaces.

Inactive Ingredient

Purified water, Carbomer 940, PEG12 - dimethicone, Propylene glycol, Aloe barbadensis leaf extract, Triethanolamine, Fragrance